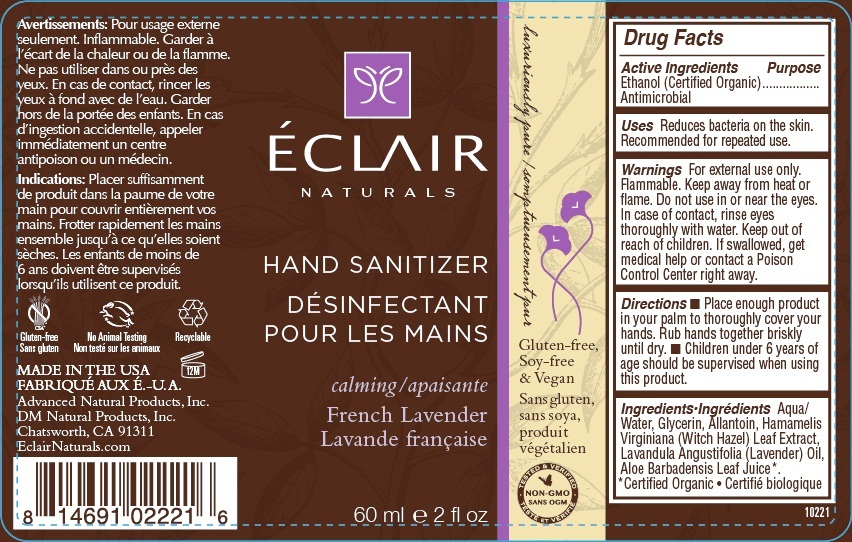 DRUG LABEL: ECLAIR NATURALS (FRENCH LAVENDER) HAND SANITIZER
NDC: 70279-221 | Form: SPRAY
Manufacturer: Dm Natural Products, Inc
Category: otc | Type: HUMAN OTC DRUG LABEL
Date: 20160116

ACTIVE INGREDIENTS: ALCOHOL 62 mL/100 mL
INACTIVE INGREDIENTS: WATER; GLYCERIN; ALLANTOIN; HAMAMELIS VIRGINIANA LEAF; LAVENDER OIL; ALOE VERA LEAF

ECLAIR NATURALS (FRENCH LAVENDER) HAND SANITIZER

Active Ingredients

Ethanol (Certified Organic) 62%

Purpose

Antimicrobial

Keep out of reach of children. If swallowed, get medical help or contact a Poison Control Center right away.

INDICATIONS AND USAGE

Uses Reduces bacteria on the skin. Recommended for repeated use.

WARNINGS

Warnings For external use only. Flammable. Keep away from heat or flame. Do not use in or near the eyes. In case of contact, rinse eyes thoroughly with water.

DOSAGE AND ADMINISTRATION

Directions • Place enough product in your palm to thoroughly cover your hands. Rub hands together briskly until dry. • Children under 6 years of age should be supervised when using this product.

INACTIVE INGREDIENT

Ingredients Aqua/Water, Glycerin , Allantoin, Hamamelis Virginiana (Witch Hazel) Leaf Extract, Lavandula Angustifolia (Lavender) Oil, Aloe Barbadensis Leaf Juice*.

*Certified Organic

Gluten-free

No Animal Testing

Recyclable

Luxuriously pure

Soy-free & Vegan

MADE IN THE USA

Advanced Natural Products, Inc.

DM Natural Products, Inc.

Chatsworth, CA 91311

EclairNaturals.com